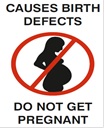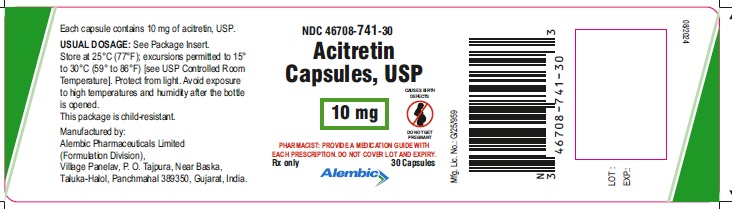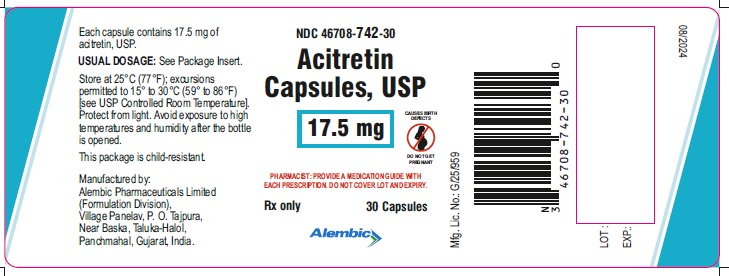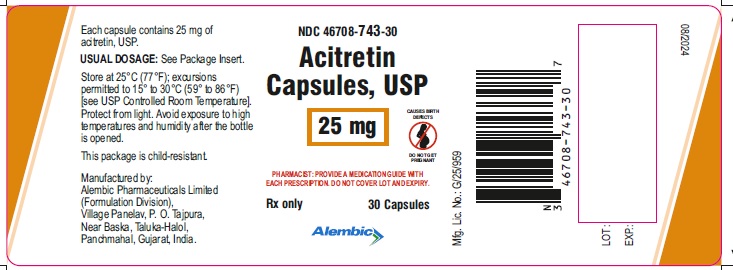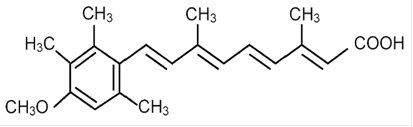 DRUG LABEL: Acitretin
NDC: 46708-741 | Form: CAPSULE
Manufacturer: Alembic Pharmaceuticals Limited
Category: prescription | Type: Human Prescription Drug Label
Date: 20240809

ACTIVE INGREDIENTS: ACITRETIN 10 mg/1 1
INACTIVE INGREDIENTS: MICROCRYSTALLINE CELLULOSE; MALTODEXTRIN; SODIUM ASCORBATE; SODIUM LAURYL SULFATE; SILICON DIOXIDE; MAGNESIUM STEARATE; GELATIN, UNSPECIFIED; FERRIC OXIDE RED; TITANIUM DIOXIDE; SHELLAC; FERROSOFERRIC OXIDE; POTASSIUM HYDROXIDE; FERRIC OXIDE YELLOW

Acitretin Capsules, USP

CONTRAINDICATIONS AND WARNINGS: Pregnancy

Acitretin must not be used by females who are pregnant, or who intend to become pregnant during therapy or at any time for at least 3 years following discontinuation of therapy. Acitretin also must not be used by females who may not use reliable contraception while undergoing treatment and for at least 3 years following discontinuation of treatment. Acitretin is a metabolite of etretinate (TEGISON), and major human fetal abnormalities have been reported with the administration of acitretin and etretinate. Potentially, any fetus exposed can be affected.

Clinical evidence has shown that concurrent ingestion of acitretin and ethanol has been associated with the formation of etretinate, which has a significantly longer elimination half-life than acitretin. Because the longer elimination half-life of etretinate would increase the duration of teratogenic potential for female patients, ethanol must not be ingested by female patients of childbearing potential either during treatment with acitretin or for 2 months after cessation of therapy. This allows for elimination of acitretin, thus removing the substrate for transesterification to etretinate. The mechanism of the metabolic process for conversion of acitretin to etretinate has not been fully defined. It is not known whether substances other than ethanol are associated with transesterification.

Acitretin has been shown to be embryotoxic and/or teratogenic in rabbits, mice, and rats at oral doses of 0.6, 3, and 15 mg per kg, respectively. These doses are approximately 0.2, 0.3, and 3 times the maximum recommended therapeutic dose, respectively, based on a mg-per-m^2 comparison.

Major human fetal abnormalities associated with acitretin and/or etretinate administration have been reported including meningomyelocele; meningoencephalocele; multiple synostoses; facial dysmorphia; syndactyly; absence of terminal phalanges; malformations of hip, ankle, and forearm; low-set ears; high palate; decreased cranial volume; cardiovascular malformation; and alterations of the skull and cervical vertebrae.

Acitretin should be prescribed only by those who have special competence in the diagnosis and treatment of severe psoriasis, are experienced in the use of systemic retinoids, and understand the risk of teratogenicity.

Because of the teratogenicity of acitretin, a program called the H.A.E.R.T. program, Healthier Acitretin Education and Remission Treatment, has been developed to educate women of childbearing potential and their healthcare providers about the serious risks associated with acitretin and to help prevent pregnancies from occurring with the use of this drug and for 3 years after its discontinuation. The H.A.E.R.T. program requirements are described below and program materials are available at https://www.alembicusa.com/AcitretinHAERT or may be requested by calling 1-866-210-9797 (see also PRECAUTIONS section).

Important Information for Women of Childbearing Potential:
Acitretin should be considered only for women with severe psoriasis unresponsive to other therapies or whose clinical condition contraindicates the use of other treatments.

Females of reproductive potential must not be given a prescription for acitretin until pregnancy is excluded. Acitretin are contraindicated in females of reproductive potential unless the patient meets ALL of the following conditions:

• Must have had 2 negative urine or serum pregnancy tests with a sensitivity of at least 25 mIU per mL before receiving the initial prescription for acitretin. The first test (a screening test) is obtained by the prescriber when the decision is made to pursue therapy with acitretin. The second pregnancy test (a confirmation test) should be done during the first 5 days of the menstrual period immediately preceding the beginning of therapy with acitretin. For patients with amenorrhea, the second test should be done at least 11 days after the last act of unprotected sexual intercourse (without using 2 effective forms of contraception [birth control] simultaneously). If the second pregnancy test is negative, initiation of treatment with acitretin should begin within 7 days of the specimen collection. Acitretin should be limited to a monthly supply.

• Must have a pregnancy test with a sensitivity of at least 25 mIU per mL repeated every month during treatment with acitretin. The patient must have a negative result from a urine or serum pregnancy test before receiving a prescription for acitretin. To encourage compliance with this recommendation, a monthly supply of the drug should be prescribed. For at least 3 years after discontinuing therapy with acitretin, a pregnancy test must be repeated every 3 months.

• Must have selected and have committed to use 2 effective forms of contraception (birth control) simultaneously, at least 1 of which must be a primary form, unless absolute abstinence is the chosen method, or the patient has undergone a hysterectomy or is clearly postmenopausal.

• Patients must use 2 effective forms of contraception (birth control) simultaneously for at least 1 month prior to initiation of therapy with acitretin, during therapy with acitretin, and for at least 3 years after discontinuing therapy with acitretin. Counseling about contraception and behaviors associated with an increased risk of pregnancy must be repeated on a monthly basis by the prescriber during therapy with acitretin and every 3 months for at least 3 years following discontinuation of acitretin.

Effective forms of contraception include both primary and secondary forms of contraception. Primary forms of contraception include: tubal ligation, partner’s vasectomy, intrauterine devices, birth control pills, and injectable/implantable/insertable/topical hormonal birth control products. Secondary forms of contraception include condoms (with or without spermicide), diaphragms and cervical caps (which must be used with a spermicide), and vaginal sponges (contains spermicide).

Any birth control method can fail. Therefore, it is critically important that women of childbearing potential use 2 effective forms of contraception (birth control) simultaneously. It has not been established if there is a pharmacokinetic interaction between acitretin and combined oral contraceptives. However, it has been established that acitretin interferes with the contraceptive effect of microdosed progestin preparations.^1 Microdosed “minipill” progestin preparations are not recommended for use with acitretin. It is not known whether other progestin¬only contraceptives, such as implants and injectables, are adequate methods of contraception during acitretin therapy. Prescribers are advised to consult the package insert of any medication administered concomitantly with hormonal contraceptives, since some medications may decrease the effectiveness of these birth control products. Patients should be prospectively cautioned not to self-medicate with the herbal supplement St. John’s wort because a possible interaction has been suggested with hormonal contraceptives based on reports of breakthrough bleeding on oral contraceptives shortly after starting St. John’s wort. Pregnancies have been reported by users of combined hormonal contraceptives who also used some form of St. John’s wort (see PRECAUTIONS).

• Must have signed a Patient Agreement/Informed Consent for Female Patients that contains warnings about the risk of potential birth defects if the fetus is exposed to acitretin, about contraceptive failure, about the fact that they must not ingest beverages or products containing ethanol while taking acitretin and for 2 months after treatment with acitretin has been discontinued, and about preventing pregnancy while taking acitretin and for at least 3 years after discontinuing acitretin.
If pregnancy does occur during therapy with acitretin or at any time for at least 3 years following discontinuation of acitretin, the prescriber and patient should discuss the possible effects on the pregnancy. The available information is as follows:

Acitretin, the active metabolite of etretinate, is teratogenic and is contraindicated during pregnancy. The risk of severe fetal malformations is well established when systemic retinoids are taken during pregnancy. Pregnancy must also be prevented after stopping acitretin therapy, while the drug is being eliminated to below a threshold blood concentration that would be associated with an increased incidence of birth defects. Because this threshold has not been established for acitretin in humans and because elimination rates vary among patients, the duration of posttherapy contraception to achieve adequate elimination cannot be calculated precisely. It is strongly recommended that contraception be continued for at least 3 years after stopping treatment with acitretin, based on the following considerations:

o In the absence of transesterification to form etretinate, greater than 98% of the acitretin would be eliminated within 2 months, assuming a mean elimination half-life of 49 hours.
o In cases where etretinate is formed, as has been demonstrated with concomitant administration of acitretin and ethanol,
♦ greater than 98% of the etretinate formed would be eliminated in 2 years, assuming a mean elimination half-life of 120 days.
♦ greater than 98% of the etretinate formed would be eliminated in 3 years, based on the longest demonstrated elimination half-life of 168 days. However, etretinate was found in plasma and subcutaneous fat in one patient reported to have had sporadic alcohol intake, 52 months after she stopped acitretin therapy.^2

• Severe birth defects have been reported where conception occurred during the time interval when the patient was being treated with acitretin and/or etretinate. In addition, severe birth defects have also been reported when conception occurred after the mother completed therapy. These cases have been reported both prospectively (before the outcome was known) and retrospectively (after the outcome was known). The events below are listed without distinction as to whether the reported birth defects are consistent with retinoid-induced embryopathy or not.

♦ There have been 318 prospectively reported cases involving pregnancies and the use of etretinate, acitretin, or both. In 238 of these cases, the conception occurred after the last dose of etretinate (103 cases), acitretin (126), or both (9). Fetal outcome remained unknown in approximately one-half of these cases, of which 62 were terminated and 14 were spontaneous abortions. Fetal outcome is known for the other 118 cases and 15 of the outcomes were abnormal (including cases of absent hand/wrist, clubfoot, GI malformation, hypocalcemia, hypotonia, limb malformation, neonatal apnea/anemia, neonatal ichthyosis, placental disorder/death, undescended testicle, and 5 cases of premature birth). In the 126 prospectively reported cases where conception occurred after the last dose of acitretin only, 43 cases involved conception at least 1 year but less than 2 years after the last dose. There were 3 reports of abnormal outcomes out of these 43 cases (involving limb malformation, GI tract malformations, and premature birth). There were only 4 cases where conception occurred at least 2 years after the last dose but there were no reports of birth defects in these cases.

♦ There is also a total of 35 retrospectively reported cases where conception occurred at least 1 year after the last dose of etretinate, acitretin, or both. From these cases there are 3 reports of birth defects when the conception occurred at least 1 year but less than 2 years after the last dose of acitretin (including heart malformations, Turner’s Syndrome, and unspecified congenital malformations) and 4 reports of birth defects when conception occurred 2 or more years after the last dose of acitretin (including foot malformation, cardiac malformations [2 cases], and unspecified neonatal and infancy disorder). There were 3 additional abnormal outcomes in cases where conception occurred 2 or more years after the last dose of etretinate (including chromosome disorder, forearm aplasia, and stillbirth).

♦ Females who have taken TEGISON (etretinate) must continue to follow the contraceptive recommendations for TEGISON. TEGISON is no longer marketed in the US; for information, call Alembic Pharmaceuticals Limited at 1-866-210-9797.
♦ Patients should not donate blood during and for at least 3 years following the completion of therapy with acitretin because women of childbearing potential must not receive blood from patients being treated with acitretin.

Important Information for Males Taking Acitretin:
Patients should not donate blood during and for at least 3 years following therapy with acitretin because women of childbearing potential must not receive blood from patients being treated with acitretin.

• Samples of seminal fluid from 3 male patients treated with acitretin and 6 male patient treated with etretinate have been assayed for the presence of acitretin. The maximum concentration of acitretin observed in the seminal fluid of these men was 12.5 ng per mL. Assuming an ejaculate volume of 10 mL, the amount of drug transferred in semen would be 125 ng, which is 1/200,000 of a single 25-mg capsule. Thus, although it appears that residual acitretin in seminal fluid poses little, if any, risk to a fetus while a male patient is taking the drug or after it is discontinued, the no-effect limit for teratogenicity is unknown and there is no registry for birth defects associated with acitretin. The available data are as follows:

There have been 25 cases of reported conception when the male partner was taking acitretin. The pregnancy outcome is known in 13 of these 25 cases. Of these, 9 reports were retrospective and 4 were prospective (meaning the pregnancy was reported prior to knowledge of the outcome)^3.

Timing of Paternal Acitretin Treatment Relative to Conception | Delivery of Healthy Neonate | Spontaneous Abortion | Induced Abortion | Total
At time of conception | 5a | 5 | 1 | 11
Discontinued ~4 weeks prior | 0 | 0 | 1b | 1
Discontinued ~6 to 8 months prior | 0 | 1 | 0 | 1

a Four of 5 cases were prospective
b With malformation pattern not typical of retinoid embryopathy (bilateral cystic hygromas of neck. hypoplasia of lungs bilateral. VSD with overriding truncus arteriosus).

For All Patients: AN ACITRETIN MEDICATION GUIDE MUST BE GIVEN TO THE PATIENT EACH TIME ACITRETIN IS DISPENSED, AS REQUIRED BY LAW.

DESCRIPTION

Acitretin, USP a retinoid, is available in 10-mg, 17.5-mg, and 25-mg gelatin capsules for oral administration. Chemically, acitretin is all-trans-9-(4-methoxy-2,3,6-trimethylphenyl)-3,7-dimethyl-2,4,6,8-nonatetraenoic acid. It is a metabolite of etretinate and is related to both retinoic acid and retinol (vitamin A). It is a yellow to greenish-yellow crystalline powder with a molecular weight of 326.44. The structural formula is:

Each capsule contains acitretin, microcrystalline cellulose, maltodextrin, sodium ascorbate, sodium lauryl sulfate, colloidal silicon dioxide and magnesium stearate.

Gelatin capsule shells contain gelatin, iron oxide yellow, iron oxide red, titanium dioxide and sodium lauryl sulfate. Additionally, 10 mg and 25 mg gelatin capsule shells contains iron oxide black.

The gelatin capsule shells are printed with edible black ink containing shellac, iron oxide black and potassium hydroxide.

FDA approved dissolution test specifications differ from USP.

CLINICAL PHARMACOLOGY

The mechanism of action of acitretin is unknown.

Pharmacokinetics: Absorption: Oral absorption of acitretin is optimal when given with food. For this reason, acitretin was given with food in all of the following trials. After administration of a single 50-mg oral dose of acitretin to 18 healthy subjects, maximum plasma concentrations ranged from 196 to 728 ng per mL (mean: 416 ng per mL) and were achieved in 2 to 5 hours (mean: 2.7 hours). The oral absorption of acitretin is linear and proportional with increasing doses from 25 to 100 mg. Approximately 72% (range: 47% to 109%) of the administered dose was absorbed after a single 50-mg dose of acitretin was given to 12 healthy subjects.

Distribution: Acitretin is more than 99.9% bound to plasma proteins, primarily albumin.

Metabolism: (See Pharmacokinetic Drug Interactions: Ethanol.) Following oral absorption, acitretin undergoes extensive metabolism and interconversion by simple isomerization to its 13-cis form (cis-acitretin). The formation of cis-acitretin relative to parent compound is not altered by dose or fed/fast conditions of oral administration of acitretin. Both parent compound and isomer are further metabolized into chain-shortened breakdown products and conjugates, which are excreted. Following multiple-dose administration of acitretin, steady-state concentrations of acitretin and cis-acitretin in plasma are achieved within approximately 3 weeks.

Elimination: The chain-shortened metabolites and conjugates of acitretin and cis-acitretin are ultimately excreted in the feces (34% to 54%) and urine (16% to 53%). The terminal elimination half-life of acitretin following multiple-dose administration is 49 hours (range: 33 to 96 hours), and that of cis-acitretin under the same conditions is 63 hours (range: 28 to 157 hours). The accumulation ratio of the parent compound is 1.2; that of cis-acitretin is 6.6.

Special Populations: Psoriasis: In an 8-week trial of acitretin pharmacokinetics in subjects with psoriasis, mean steady-state trough concentrations of acitretin increased in a dose-proportional manner with dosages ranging from 10 to 50 mg daily. Acitretin plasma concentrations were nonmeasurable (<4 ng per mL) in all subjects 3 weeks after cessation of therapy.

Elderly: In a multiple-dose trial in healthy young (n = 6) and elderly (n = 8) subjects, a 2-fold increase in acitretin plasma concentrations were seen in elderly subjects, although the elimination half-life did not change.

Renal Failure: Plasma concentrations of acitretin were significantly (59.3%) lower in subjects with end-stage renal failure (n = 6) when compared with age-matched controls, following single 50-mg oral doses. Acitretin was not removed by hemodialysis in these subjects.

Pharmacokinetic Drug Interactions (see also boxed CONTRAINDICATIONS AND WARNINGS and PRECAUTIONS: Drug Interactions): In studies of in vivo pharmacokinetic drug interactions, no interaction was seen between acitretin and cimetidine, digoxin, phenprocoumon, or glyburide.

Ethanol: Clinical evidence has shown that etretinate (a retinoid with a much longer half-life, see below) can be formed with concurrent ingestion of acitretin and ethanol. In a 2-way crossover trial, all 10 subjects formed etretinate with concurrent ingestion of a single 100-mg oral dose of acitretin during a 3-hour period of ethanol ingestion (total ethanol, approximately 1.4 g per kg body weight). A mean peak etretinate concentration of 59 ng per mL (range: 22 to 105 ng per mL) was observed, and extrapolation of AUC values indicated that the formation of etretinate in this trial was comparable to a single 5-mg oral dose of etretinate. There was no detectable formation of etretinate when a single 100-mg oral dose of acitretin was administered without concurrent ethanol ingestion, although the formation of etretinate without concurrent ethanol ingestion cannot be excluded (see boxed CONTRAINDICATIONS AND WARNINGS). Of 93 evaluable psoriatic subjects on acitretin therapy in several foreign trials (10 to 80 mg per day), 16% had measurable etretinate levels (>5 ng per mL).

Etretinate has a much longer elimination half-life compared with that of acitretin. In one trial the apparent mean terminal half-life after 6 months of therapy was approximately 120 days (range: 84 to 168 days). In another trial of 47 subjects treated chronically with etretinate, 5 had detectable serum drug levels (in the range of 0.5 to 12 ng per mL) 2.1 to 2.9 years after therapy was discontinued. The long half-life appears to be due to storage of etretinate in adipose tissue.

Progestin-only Contraceptives: It has not been established if there is a pharmacokinetic interaction between acitretin and combined oral contraceptives. However, it has been established that acitretin interferes with the contraceptive effect of microdosed progestin preparations.^1 Microdosed “minipill” progestin preparations are not recommended for use with acitretin. It is not known whether other progestin-only contraceptives, such as implants and injectables, are adequate methods of contraception during acitretin therapy.

CLINICAL STUDIES

In 2 double-blind, placebo-controlled trials, acitretin was administered once daily to subjects with severe psoriasis (e.g., covering at least 10% to 20% of the body surface area). At 8 weeks (see Table 1) subjects treated in Trial A with 50 mg of acitretin per day showed significant improvements (P ≤0.05) relative to baseline and to placebo in the physician’s global evaluation and in the mean ratings of severity of psoriasis (scaling, thickness, and erythema). In Trial B, differences from baseline and from placebo were statistically significant (P ≤0.05) for all variables at both the 25-mg and 50-mg doses; it should be noted for Trial B that no statistical adjustment for multiplicity was carried out.

Table 1. Summary of the Efficacy Results of the 8-Week Double-Blind Phase of Trials A and B of Acitretin

Efficacy Variables | Trial A |  | Trial B
Efficacy Variables | Total Daily Dose |  | Total Daily Dose
Efficacy Variables | Placebo (N = 29) | 50 mg (N = 29) | Placebo (N = 72) | 25 mg (N = 74) | 50 mg (N = 71)
Physician’s Global Evaluation
Baseline | 4.62 | 4.55 | 4.43 | 4.37 | 4.49
Mean Change After 8 Weeks | −0.29 | −2a | −0.06 | −1.06a | −1.57a
Scaling
Baseline | 4.1 | 3.76 | 3.97 | 4.11 | 4.1
Mean Change After 8 Weeks | −0.22 | −1.62a | −0.21 | −1.5a | −1.78a
Thickness
Baseline | 4.1 | 4.1 | 4.03 | 4.11 | 4.2
Mean Change After 8 Weeks | −0.39 | −2.1a | −0.18 | −1.43a | −2.11a
Erythema
Baseline | 4.21 | 4.59 | 4.42 | 4.24 | 4.45
Mean Change After 8 Weeks | −0.33 | −2.1a | −0.37 | −1.12a | −1.65a

a Values were statistically significantly different from placebo and from baseline (P ≤0.05). No adjustment for multiplicity was done for Trial B.

The efficacy variables consisted of: the mean severity rating of scale, lesion thickness, erythema, and the physician’s global evaluation of the current status of the disease. Ratings of scaling, erythema, and lesion thickness, and the ratings of the global assessments were made using a 7-point scale (0 = none, 1 = trace, 2 = mild, 3 = mild-moderate, 4 = moderate, 5 = moderate-severe, 6 = severe).

A subset of 141 subjects from both pivotal Trials A and B continued to receive acitretin in an open fashion for up to 24 weeks. At the end of the treatment period, all efficacy variables, as indicated in Table 2, were significantly improved (P ≤0.01) from baseline, including extent of psoriasis, mean ratings of psoriasis severity, and physician’s global evaluation.

Table 2. Summary of the First Course of Therapy with Acitretin (24 Weeks)

Variables | Trial A | Trial B
Mean Total Daily Dose of Acitretin (mg) | 42.8 | 43.1
Mean Duration of Therapy (Weeks) | 21.1 | 22.6
Physician’s Global Evaluation | N = 39 | N = 98
Baseline | 4.51 | 4.43
Mean Change from Baseline | −2.26a | −2.6a
Scaling | N = 59 | N = 132
Baseline | 3.97 | 4.07
Mean Change from Baseline | −2.15a | −2.42a
Thickness | N = 59 | N = 132
Baseline | 4 | 4.12
Mean Change from Baseline | −2.44a | −2.66a
Erythema | N = 59 | N = 132
Baseline | 4.35 | 4.33
Mean Change from Baseline | −2.31a | −2.29a

a Indicates that the difference from baseline was statistically significant (P ≤0.01).

The efficacy variables consisted of: the mean severity rating of scale, lesion thickness, erythema, and the physician’s global evaluation of the current status of the disease. Ratings of scaling, erythema, and lesion thickness, and the ratings of the global assessments were made using a 7-point scale (0 = none, 1 = trace, 2 = mild, 3 = mild-moderate, 4 = moderate, 5 = moderate-severe, 6 = severe).

All efficacy variables improved significantly in a subset of 55 subjects from Trial A treated for a second, 6-month maintenance course of therapy (for a total of 12 months of treatment); a small subset of subjects (n = 4) from Trial A continued to improve after a third 6-month course of therapy (for a total of 18 months of treatment).

INDICATIONS AND USAGE

Acitretin capsules are indicated for the treatment of severe psoriasis in adults. Because of significant adverse effects associated with its use, acitretin capsules should be prescribed only by those knowledgeable in the systemic use of retinoids. In females of reproductive potential, acitretin capsules should be reserved for non-pregnant patients who are unresponsive to other therapies or whose clinical condition contraindicates the use of other treatments (see boxed CONTRAINDICATIONS AND WARNINGS — acitretin capsules can cause severe birth defects).

Most patients experience relapse of psoriasis after discontinuing therapy. Subsequent courses, when clinically indicated, have produced efficacy results similar to the initial course of therapy.

CONTRAINDICATIONS

Pregnancy : See boxed CONTRAINDICATIONS AND WARNINGS.

Acitretin is contraindicated in patients with severely impaired liver or kidney function and in patients with chronic abnormally elevated blood lipid values (see boxed WARNINGS: Hepatotoxicity, WARNINGS: Lipids and Possible Cardiovascular Effects, and PRECAUTIONS).

An increased risk of hepatitis has been reported to result from combined use of methotrexate and etretinate. Consequently, the combination of methotrexate with acitretin is also contraindicated (see PRECAUTIONS: Drug Interactions).

Since both acitretin and tetracyclines can cause increased intracranial pressure, their combined use is contraindicated (see WARNINGS: Pseudotumor Cerebri).

Acitretin is contraindicated in cases of hypersensitivity (e.g., angioedema, urticaria) to the preparation (acitretin or excipients) or to other retinoids.

WARNINGS

(See also boxed CONTRAINDICATIONS AND WARNINGS.)

Hepatotoxicity: Of the 525 subjects treated in US clinical trials, 2 had clinical jaundice with elevated serum bilirubin and transaminases considered related to treatment with acitretin. Liver function test results in these subjects returned to normal after acitretin was discontinued. Two of the 1,289 subjects treated in European clinical trials developed biopsy-confirmed toxic hepatitis. A second biopsy in one of these subjects revealed nodule formation suggestive of cirrhosis. One subject in a Canadian clinical trial of 63 subjects developed a 3-fold increase of transaminases. A liver biopsy of this subject showed mild lobular disarray, multifocal hepatocyte loss, and mild triaditis of the portal tracts compatible with acute reversible hepatic injury. The subject's transaminase levels returned to normal 2 months after acitretin was discontinued.
The potential of therapy with acitretin to induce hepatotoxicity was prospectively evaluated using liver biopsies in an open-label trial of 128 subjects. Pretreatment and posttreatment biopsies were available for 87 subjects. A comparison of liver biopsy findings before and after therapy revealed 49 (58%) subjects showed no change, 21 (25%) improved, and 14 (17%) subjects had a worsening of their liver biopsy status. For 6 subjects, the classification changed from class 0 (no pathology) to class I (normal fatty infiltration; nuclear variability and portal inflammation; both mild); for 7 subjects, the change was from class I to class II (fatty infiltration, nuclear variability, portal inflammation, and focal necrosis; all moderate to severe); and for 1 subject, the change was from class II to class IIIb (fibrosis, moderate to severe). No correlation could be found between liver function test result abnormalities and the change in liver biopsy status, and no cumulative dose relationship was found.
Elevations of AST (SGOT), ALT (SGPT), GGT (GGTP), or LDH have occurred in approximately 1 in 3 subjects treated with acitretin. Of the 525 subjects treated in clinical trials in the US, treatment was discontinued in 20 (3.8%) due to elevated liver function test results. If hepatotoxicity is suspected during treatment with acitretin, the drug should be discontinued and the etiology further investigated.
Ten of 652 subjects treated in US clinical trials of etretinate, of which acitretin is the active metabolite, had clinical or histologic hepatitis considered to be possibly or probably related to etretinate treatment.
There have been reports of hepatitis-related deaths worldwide; a few of these subjects had received etretinate for a month or less before presenting with hepatic symptoms or signs.

Skeletal Abnormalities

In adults receiving long-term treatment with acitretin, appropriate examinations should be periodically performed in view of possible ossification abnormalities (see ADVERSE REACTIONS). Because the frequency and severity of iatrogenic bony abnormality in adults is low, periodic radiography is only warranted in the presence of symptoms or long-term use of acitretin. If such disorders arise, the continuation of therapy should be discussed with the patient on the basis of a careful risk/benefit analysis. In clinical trials with acitretin, subjects were prospectively evaluated for evidence of development or change in bony abnormalities of the vertebral column, knees, and ankles.

Of 380 subjects treated with acitretin, 15% had preexisting abnormalities of the spine which showed new changes or progression of preexisting findings. Changes included degenerative spurs, anterior bridging of spinal vertebrae, diffuse idiopathic skeletal hyperostosis, ligament calcification, and narrowing and destruction of a cervical disc space. De novo changes (formation of small spurs) were seen in 3 subjects after 1½ to 2½ years.

Six of 128 subjects treated with acitretin showed abnormalities in the knees and ankles before treatment that progressed during treatment. In 5, these changes involved the formation of additional spurs or enlargement of existing spurs. The sixth subject had degenerative joint disease which worsened. No subjects developed spurs de novo. Clinical complaints did not predict radiographic changes.

Lipids and Possible Cardiovascular Effects

Blood lipid determinations should be performed before acitretin is administered and again at intervals of 1 to 2 weeks until the lipid response to the drug is established, usually within 4 to 8 weeks. In subjects receiving acitretin during clinical trials, 66% and 33% experienced elevation in triglycerides and cholesterol, respectively. Decreased high density lipoproteins (HDL) occurred in 40% of subjects. These effects of acitretin were generally reversible upon cessation of therapy.

Subjects with an increased tendency to develop hypertriglyceridemia included those with disturbances of lipid metabolism, diabetes mellitus, obesity, increased alcohol intake, or a familial history of these conditions. Because of the risk of hypertriglyceridemia, serum lipids must be more closely monitored in high-risk patients and during long-term treatment.

Hypertriglyceridemia and lowered HDL may increase a patient’s cardiovascular risk status. Although no causal relationship has been established, there have been postmarketing reports of acute myocardial infarction or thromboembolic events in patients on therapy with acitretin. In addition, elevation of serum triglycerides to greater than 800 mg per dL has been associated with fatal fulminant pancreatitis. Therefore, dietary modifications, reduction in dose of acitretin, or drug therapy should be employed to control significant elevations of triglycerides. If, despite these measures, hypertriglyceridemia and low HDL levels persist, the discontinuation of acitretin should be considered.

Ophthalmologic Effects

The eyes and vision of 329 subjects treated with acitretin were examined by ophthalmologists. The findings included dry eyes (23%), irritation of eyes (9%), and brow and lash loss (5%). The following were reported in less than 5% of subjects: Bell’s palsy, blepharitis and/or crusting of lids, blurred vision, conjunctivitis, corneal epithelial abnormality, cortical cataract, decreased night vision, diplopia, itchy eyes or eyelids, nuclear cataract, pannus, papilledema, photophobia, posterior subcapsular cataract, recurrent sties, and subepithelial corneal lesions.

Any patient treated with acitretin who is experiencing visual difficulties should discontinue the drug and undergo ophthalmologic evaluation.

Pancreatitis

Lipid elevations occur in 25% to 50% of subjects treated with acitretin. Triglyceride increases sufficient to be associated with pancreatitis are much less common, although fatal fulminant pancreatitis has been reported. There have been rare reports of pancreatitis during therapy with acitretin in the absence of hypertriglyceridemia.

Pseudotumor Cerebri

Acitretin and other retinoids administered orally have been associated with cases of pseudotumor cerebri (benign intracranial hypertension). Some of these events involved concomitant use of isotretinoin and tetracyclines. However, the event seen in a single patient receiving acitretin was not associated with tetracycline use. Early signs and symptoms include papilledema, headache, nausea and vomiting, and visual disturbances. Patients with these signs and symptoms should be examined for papilledema and, if present, should discontinue acitretin immediately and be referred for neurological evaluation and care. Since both acitretin and tetracyclines can cause increased intracranial pressure, their combined use is contraindicated (see CONTRAINDICATIONS).

Capillary Leak Syndrome

Capillary leak syndrome, a potential manifestation of retinoic acid syndrome, has been reported in patients receiving acitretin. Features of this syndrome may include localized or generalized edema with secondary weight gain, fever, and hypotension. Rhabdomyolysis and myalgias have been reported in association with capillary leak syndrome, and laboratory tests may reveal neutrophilia, hypoalbuminemia, and an elevated hematocrit. Discontinue acitretin if capillary leak syndrome develops during therapy.

Exfoliative Dermatitis/Erythroderma

Exfoliative dermatitis/erythroderma has been reported in patients receiving acitretin. Discontinue acitretin if exfoliative dermatitis/erythroderma occurs during therapy.

PRECAUTIONS

A description of the H.A.E.R.T. materials is provided below. The main goals of the materials are to explain the program requirements, to reinforce the educational messages, and to assess program effectiveness.

The H.A.E.R.T. booklet includes:

- The H.A.E.R.T. Patient Brochure: information on the program requirements, risks of acitretin, and the types of contraceptive methods
- The Patient Agreement/Informed Consent for Female Patients form
- Medication Guide

H.A.E.R.T. Program materials are available at https://www.alembicusa.com/AcitretinHAERT or may be requested by calling 1-866-210-9797.

Information for Patients

(See Medication Guide for all patients and Patient Agreement/Informed Consent for Female Patients at end of professional labeling).

Patients should be instructed to read the Medication Guide supplied as required by law when acitretin is dispensed.

Females of Reproductive Potential: Acitretin can cause severe birth defects. Female patients must not be pregnant when therapy with acitretin is initiated, they must not become pregnant while taking acitretin and for at least 3 years after stopping acitretin, so that the drug can be eliminated to below a blood concentration that would be associated with an increased incidence of birth defects. Because this threshold has not been established for acitretin in humans and because elimination rates vary among patients, the duration of posttherapy contraception to achieve adequate elimination cannot be calculated precisely (see boxed CONTRAINDICATIONS AND WARNINGS).

Females of reproductive potential should also be advised that they must not ingest beverages or products containing ethanol while taking acitretin and for 2 months after acitretin has been discontinued. This allows for elimination of the acitretin which can be converted to etretinate in the presence of alcohol.

Female patients should be advised that any method of birth control can fail, including tubal ligation, and that microdosed progestin “minipill” preparations are not recommended for use with acitretin (see CLINICAL PHARMACOLOGY: Pharmacokinetic Drug Interactions). Data from one patient who received a very low-dosed progestin contraceptive (levonorgestrel 0.03 mg) had a significant increase of the progesterone level after 3 menstrual cycles during acitretin treatment.^2

Female patients should be advised to contact their physician, women’s health centers, pharmacies, or hospital emergency rooms for information about how to obtain Emergency Contraception if sexual intercourse occurs without using 2 effective forms of contraception simultaneously. A 24-hour, toll-free number (1-800-724-4242) is also available for patients to receive automated birth control and emergency contraception information.

Female patients should sign a consent form prior to beginning therapy with acitretin (see boxed CONTRAINDICATIONS AND WARNINGS).

Nursing Mothers: Studies on lactating rats have shown that etretinate is excreted in the milk. There is one prospective case report where acitretin is reported to be excreted in human milk. Therefore, nursing mothers should not receive acitretin prior to or during nursing because of the potential for serious adverse reactions in nursing infants.

All Patients: Depression and/or other psychiatric symptoms such as aggressive feelings or thoughts of self-harm have been reported. These events, including self-injurious behavior, have been reported in patients taking other systemically administered retinoids, as well as in patients taking acitretin. Since other factors may have contributed to these events, it is not known if they are related to acitretin. Patients should be counseled to stop taking acitretin and notify their prescriber immediately if they experience psychiatric symptoms.

Patients should be advised that a transient worsening of psoriasis is sometimes seen during the initial treatment period. Patients should be advised that they may have to wait 2 to 3 months before they get the full benefit of acitretin, although some patients may achieve significant improvements within the first 8 weeks of treatment as demonstrated in clinical trials.

Decreased night vision has been reported during therapy with acitretin. Patients should be advised of this potential problem and warned to be cautious when driving or operating any vehicle at night. Visual problems should be carefully monitored (see WARNINGS and ADVERSE REACTIONS). Patients should be advised that they may experience decreased tolerance to contact lenses during the treatment period and sometimes after treatment has stopped.

Patients should not donate blood during and for at least 3 years following therapy because acitretin can cause birth defects and women of childbearing potential must not receive blood from patients being treated with acitretin.

Because of the relationship of acitretin to vitamin A, patients should be advised against taking vitamin A supplements in excess of minimum recommended daily allowances to avoid possible additive toxic effects.

Patients should avoid the use of sun lamps and excessive exposure to sunlight (non-medical UV exposure) because the effects of UV light are enhanced by retinoids.

Patients should be advised that they must not give their acitretin to any other person.

For Prescribers: Acitretin has not been studied in and is not indicated for treatment of acne.

Phototherapy: Significantly lower doses of phototherapy are required when acitretin is used because effects on the stratum corneum induced by acitretin can increase the risk of erythema (burning) (see DOSAGE AND ADMINISTRATION).

Drug Interactions

Ethanol: Clinical evidence has shown that etretinate can be formed with concurrent ingestion of acitretin and ethanol (see boxed CONTRAINDICATIONS AND WARNINGS and CLINICAL PHARMACOLOGY: Pharmacokinetics).

Glyburide: In a trial of 7 healthy male volunteers, acitretin treatment potentiated the blood glucose-lowering effect of glyburide (a sulfonylurea similar to chlorpropamide) in 3 of the 7 subjects. Repeating the trial with 6 healthy male volunteers in the absence of glyburide did not detect an effect of acitretin on glucose tolerance. Careful supervision of diabetic patients under treatment with acitretin is recommended (see CLINICAL PHARMACOLOGY: Pharmacokinetics and DOSAGE AND ADMINISTRATION).

Hormonal Contraceptives: It has not been established if there is a pharmacokinetic interaction between acitretin and combined oral contraceptives. However, it has been established that acitretin interferes with the contraceptive effect of microdosed progestin “minipill” preparations. Microdosed “minipill” progestin preparations are not recommended for use with acitretin (see CLINICAL PHARMACOLOGY: Pharmacokinetic Drug Interactions). It is not known whether other progestin-only contraceptives, such as implants and injectables, are adequate methods of contraception during acitretin therapy.

Methotrexate: An increased risk of hepatitis has been reported to result from combined use of methotrexate and etretinate. Consequently, the combination of methotrexate with acitretin is also contraindicated (see CONTRAINDICATIONS).

Phenytoin: If acitretin is given concurrently with phenytoin, the protein binding of phenytoin may be reduced.

Tetracyclines: Since both acitretin and tetracyclines can cause increased intracranial pressure, their combined use is contraindicated (see CONTRAINDICATIONS and WARNINGS: Pseudotumor Cerebri).

Vitamin A and Oral Retinoids: Concomitant administration of vitamin A and/or other oral retinoids with acitretin must be avoided because of the risk of hypervitaminosis A.

Other: There appears to be no pharmacokinetic interaction between acitretin and cimetidine, digoxin, or glyburide. Investigations into the effect of acitretin on the protein binding of anticoagulants of the coumarin type (warfarin) revealed no interaction.

Laboratory Tests

If significant abnormal laboratory results are obtained, either dosage reduction with careful monitoring or treatment discontinuation is recommended, depending on clinical judgment.

Blood Sugar: Some patients receiving retinoids have experienced problems with blood sugar control. In addition, new cases of diabetes have been diagnosed during retinoid therapy, including diabetic ketoacidosis. In diabetics, blood-sugar levels should be monitored very carefully.

Lipids: In clinical trials, the incidence of hypertriglyceridemia was 66%, hypercholesterolemia was 33%, and that of decreased HDL was 40%. Pretreatment and follow-up measurements should be obtained under fasting conditions. It is recommended that these tests be performed weekly or every other week until the lipid response to acitretin has stabilized (see WARNINGS).

Liver Function Tests: Elevations of AST (SGOT), ALT (SGPT), or LDH were experienced by approximately 1 in 3 patients treated with acitretin. It is recommended that these tests be performed prior to initiation of therapy with acitretin, at 1- to 2-week intervals until stable, and thereafter at intervals as clinically indicated (see CONTRAINDICATIONS and boxed WARNINGS).

Carcinogenesis, Mutagenesis, Impairment of Fertility

Carcinogenesis: A carcinogenesis study of acitretin in Wistar rats, at doses up to 2 mg per kg per day administered 7 days per week for 104 weeks, has been completed. There were no neoplastic lesions observed that were considered to have been related to treatment with acitretin. An 80-week carcinogenesis study in mice has been completed with etretinate, the ethyl ester of acitretin. Blood level data obtained during this study demonstrated that etretinate was metabolized to acitretin and that blood levels of acitretin exceeded those of etretinate at all times studied. In the etretinate study, an increased incidence of blood vessel tumors (hemangiomas and hemangiosarcomas at several different sites) was noted in male, but not female, mice at doses approximately one-half the maximum recommended human therapeutic dose based on a mg-per-m^2 comparison.

Mutagenesis: Acitretin was evaluated for mutagenic potential in the Ames test, in the Chinese hamster (V79/HGPRT) assay, in unscheduled DNA synthesis assays using rat hepatocytes and human fibroblasts, and in an in vivo mouse micronucleus assay. No evidence of mutagenicity of acitretin was demonstrated in any of these assays.

Impairment of Fertility: In a fertility study in rats, the fertility of treated animals was not impaired at the highest dosage of acitretin tested, 3 mg per kg per day (approximately one-half the maximum recommended therapeutic dose based on a mg-per-m^2 comparison). Chronic toxicity studies in dogs revealed testicular changes (reversible mild to moderate spermatogenic arrest and appearance of multinucleated giant cells) in the highest dosage group (50 then 30 mg per kg per day).

No decreases in sperm count or concentration and no changes in sperm motility or morphology were noted in 31 men (17 psoriatic subjects, 8 subjects with disorders of keratinization, and 6 healthy volunteers) given 30 to 50 mg per day of acitretin for at least 12 weeks. In these trials, no deleterious effects were seen on either testosterone production, LH, or FSH in any of the 31 men.^4-6 No deleterious effects were seen on the hypothalamic-pituitary axis in any of the 18 men where it was measured.^4,5

Pregnancy

Teratogenic Effects: (see boxed CONTRAINDICATIONS AND WARNINGS).

In a study in which acitretin was administered to male rats only at a dosage of 5 mg per kg per day for 10 weeks (approximate duration of one spermatogenic cycle) prior to and during mating with untreated female rats, no teratogenic effects were observed in the progeny (see boxed CONTRAINDICATIONS AND WARNINGS for information about male use of acitretin).

Nonteratogenic Effects: In rats dosed at 3 mg per kg per day (approximately one-half the maximum recommended therapeutic dose based on a mg-per-m^2 comparison), slightly decreased pup survival and delayed incisor eruption were noted. At the next lowest dose tested, 1 mg per kg per day, no treatment-related adverse effects were observed.

Pediatric Use

Safety and effectiveness in pediatric patients have not been established. No clinical trials have been conducted in pediatric subjects. Ossification of interosseous ligaments and tendons of the extremities, skeletal hyperostoses, decreases in bone mineral density, and premature epiphyseal closure have been reported in children taking other systemic retinoids, including etretinate, a metabolite of acitretin. A causal relationship between these effects and acitretin has not been established. While it is not known that these occurrences are more severe or more frequent in children, there is special concern in pediatric patients because of the implications for growth potential (see WARNINGS: Hyperostosis).

Geriatric Use

Clinical trials of acitretin did not include sufficient numbers of subjects aged 65 and over to determine whether they respond differently than younger subjects. Other reported clinical experience has not identified differences in responses between the elderly and younger subjects. In general, dose selection for an elderly patient should be cautious, usually starting at the low end of the dosing range, reflecting the greater frequency of decreased hepatic, renal, or cardiac function, and of concomitant disease or other drug therapy. A 2-fold increase in acitretin plasma concentrations was seen in healthy elderly subjects compared with young subjects, although the elimination half-life did not change (see CLINICAL PHARMACOLOGY: Special Populations).

ADVERSE REACTIONS

Hypervitaminosis A produces a wide spectrum of signs and symptoms primarily of the mucocutaneous, musculoskeletal, hepatic, neuropsychiatric, and central nervous systems. Many of the clinical adverse reactions reported to date with administration of acitretin resemble those of the hypervitaminosis A syndrome.
Adverse Events/Postmarketing Reports
In addition to the events listed in the tables for the clinical trials, the following adverse events have been identified during postapproval use of acitretin. Because these events are reported voluntarily from a population of uncertain size, it is not always possible to reliably estimate their frequency or establish a causal relationship to drug exposure.
Cardiovascular: Acute myocardial infarction, thromboembolism (see WARNINGS), stroke.
Immune System Disorders: Hypersensitivity, including angioedema and urticaria (see CONTRAINDICATIONS).
Nervous System: Myopathy with peripheral neuropathy has been reported during therapy with acitretin. Both conditions improved with discontinuation of the drug.
Psychiatric: Aggressive feelings and/or suicidal thoughts have been reported. These events, including self-injurious behavior, have been reported in patients taking other systemically administered retinoids, as well as in patients taking acitretin. Since other factors may have contributed to these events, it is not known if they are related to acitretin (see PRECAUTIONS).
Reproductive: Vulvo-vaginitis due to Candida albicans.
Skin and Appendages: Thinning of the skin, skin fragility, and scaling may occur all over the body, particularly on the palms and soles; nail fragility is frequently observed. Madarosis and exfoliative dermatitis/erythroderma have been reported (see WARNINGS).
Vascular Disorders: Capillary leak syndrome (see WARNINGS).

Clinical Trials
During clinical trials with acitretin, 513 of 525 (98%) subjects reported a total of 3,545 adverse events. One-hundred sixteen subjects (22%) left trials prematurely, primarily because of adverse experiences involving the mucous membranes and skin. Three subjects died. Two of the deaths were not drug-related (pancreatic adenocarcinoma and lung cancer); the other subject died of an acute myocardial infarction, considered remotely related to drug therapy. In clinical trials, acitretin was associated with elevations in liver function test results or triglyceride levels and hepatitis.

The tables below list by body system and frequency the adverse events reported during clinical trials of 525 subjects with psoriasis.
Table 3. Adverse Events Frequently Reported during Clinical Trials Percent of Subjects Reporting (N = 525)

Body System | >75% | 50% to 75% | 25% to 50% | 10% to 25%
CNS |  |  |  | Rigors
Eye Disorders |  |  |  | Xerophthalmia
Mucous Membranes | Cheilitis |  | Rhinitis | Dry mouth Epistaxis
Musculoskeletal |  |  |  | Arthralgia Spinal hyperostosis (progression of existing lesions)
Skin and Appendages |  | Alopecia Skin peeling | Dry skin Nail disorder Pruritus | Erythematous rash Hyperesthesia Paresthesia Paronychia Skin atrophy Sticky skin

Table 4. Adverse Events Less Frequently Reported during Clinical Trials (Some of Which May Bear No Relationship to Therapy)
Percent of Subjects Reporting (N = 525)

Body System | 1% to 10% |  | <1%
Body as a Whole | Anorexia Edema Fatigue Hot flashes Increased appetite |  | Alcohol intolerance Dizziness Fever Influenza-like symptoms | Malaise Moniliasis Muscle weakness Weight increase
Cardiovascular | Flushing |  | Chest pain Cyanosis Increased bleeding time | Intermittent claudication Peripheral ischemia
CNS (also see Psychiatric) | Headache Pain |  | Abnormal gait Migraine Neuritis | Pseudotumor cerebri (intracranial hypertension)
Eye Disorders | Abnormal/ blurred vision Blepharitis Conjunctivitis/ irritation Corneal epithelial abnormality | Decreased night vision/ night blindness Eye abnormality Eye pain Photophobia | Abnormal lacrimation Chalazion Conjunctival hemorrhage Corneal ulceration Diplopia Ectropion | Itchy eyes and lids Papilledema Recurrent sties Subepithelial corneal lesions
Gastrointestinal | Abdominal pain Diarrhea Nausea Tongue disorder |  | Constipation Dyspepsia Esophagitis Gastritis Gastroenteritis | Glossitis Hemorrhoids Melena Tenesmus Tongue ulceration
Liver and Biliary |  |  | Hepatic function abnormal Hepatitis Jaundice
Mucous Membranes | Gingival bleeding Gingivitis Increased saliva | Stomatitis Thirst Ulcerative stomatitis | Altered saliva Hemorrhage Anal disorder Pharyngitis Gum hyperplasia
Musculoskeletal | Arthritis Arthrosis Back pain Hypertonia Myalgia | Osteodynia Peripheral joint hyperostosis (progression of existing lesions) | Bone disorder Olecranon bursitis Spinal hyperostosis (new lesions) Tendonitis
Psychiatric | Depression Insomnia Somnolence |  | Anxiety Dysphonia Libido decreased Nervousness
Reproductive |  |  | Atrophic vaginitis Leukorrhea
Respiratory | Sinusitis |  | Coughing Increased sputum Laryngitis
Skin and Appendages | Abnormal skin odor Abnormal hair texture Bullous eruption Cold/clammy skin Dermatitis Increased sweating Infection | Psoriasiform rash Purpura Pyogenic granuloma Rash Seborrhea Skin fissures Skin ulceration Sunburn | Acne Breast pain Cyst Eczema Fungal infection Furunculosis Hair discoloration Herpes simplex Hyperkeratosis Hypertrichosis Hypoesthesia Impaired healing Otitis media |  | Otitis externa Photosensitivity reaction Psoriasis aggravated Scleroderma Skin nodule Skin hypertrophy Skin disorder Skin irritation Sweat gland disorder Urticaria Verrucae
Special Senses/ Other | Earache Taste perversion Tinnitus |  | Ceruminosis Deafness Taste loss
Urinary |  |  | Abnormal urine Dysuria Penis disorder

Laboratory: Therapy with acitretin induces changes in liver function tests in a significant number of patients. Elevations of AST (SGOT), ALT (SGPT) or LDH were experienced by approximately 1 in 3 subjects treated with acitretin. In most subjects, elevations were slight to moderate and returned to normal either during continuation of therapy or after cessation of treatment. In subjects receiving acitretin during clinical trials, 66% and 33% experienced elevation in triglycerides and chlesterol, respectively. Decreased high density lipoproteins (HDL) occurred in 40% (see WARNINGS). Transient, usually reversible elevations of alkaline phosphatase have been observed.

Table 5 lists the laboratory abnormalities reported during clinical trials.

Table 5. Abnormal Laboratory Test Results Reported during Clinical Trials Percent of Subjects Reporting

Body System | 50% to 75% | 25% to 50% | 10% to 25% | 1% to 10%
Electrolytes |  |  | Increased: –Phosphorus –Potassium –Sodium Increased and decreased: –Magnesium | Decreased: –Phosphorus –Potassium –Sodium Increased and decreased: –Calcium –Chloride
Hematologic |  | Increased: –Reticulocytes | Decreased: –Hematocrit –Hemoglobin –WBC Increased: –Haptoglobin –Neutrophils –WBC | Increased: –Bands –Basophils –Eosinophils –Hematocrit –Hemoglobin –Lymphocytes –Monocytes Decreased: –Haptoglobin –Lymphocytes –Neutrophils –Reticulocytes Increased or decreased: –Platelets –RBC
Hepatic |  | Increased: –Cholesterol –LDH –SGOT –SGPT Decreased: –HDL cholesterol | Increased: –Alkaline phosphatase –Direct bilirubin –GGTP | Increased: –Globulin –Total bilirubin –Total protein Increased and decreased: –Serum albumin
Miscellaneous | Increased: –Triglycerides | Increased: –CPK –Fasting blood sugar | Decreased: –Fasting blood sugar –High occult blood | Increased and decreased: –Iron
Renal |  |  | Increased: –Uric acid | Increased: –BUN –Creatinine
Urinary |  | WBC in urine | Acetonuria Hematuria RBC in urine | Glycosuria Proteinuria

To report SUSPECTED ADVERSE REACTIONS, contact FDA at 1-800-FDA-1088 or www.fda.gov/medwatch.

OVERDOSAGE

In the event of acute overdosage, acitretin must be withdrawn at once. Symptoms of overdose are identical to acute hypervitaminosis A (e.g., headache and vertigo). The acute oral toxicity (LD50) of acitretin in both mice and rats was greater than 4,000 mg per kg.

In one reported case of overdose, a 32-year-old male with Darier’s disease took 21 x 25-mg capsules (525-mg single dose). He vomited several hours later but experienced no other ill effects.

All female patients of childbearing potential who have taken an overdose of acitretin must:

1) Have a pregnancy test at the time of overdose; 2) Be counseled as per the boxed CONTRAINDICATIONS AND WARNINGS and PRECAUTIONS sections regarding birth defects and contraceptive use for at least 3 years’ duration after the overdose.

DOSAGE AND ADMINISTRATION

There is intersubject variation in the pharmacokinetics, clinical efficacy, and incidence of side effects with acitretin capsules. A number of the more common side effects are dose-related. Individualization of dosage is required to achieve sufficient therapeutic response while minimizing side effects. Therapy with acitretin capsules should be initiated at 25 to 50 mg per day, given as a single dose with the main meal. Maintenance doses of 25 to 50 mg per day may be given dependent upon an individual patient’s response to initial treatment. Relapses may be treated as outlined for initial therapy.

When acitretin capsules are used with phototherapy, the prescriber should decrease the phototherapy dose, dependent on the patient’s individual response (see PRECAUTIONS: General).

Females who have taken TEGISON (etretinate) must continue to follow the contraceptive recommendations for TEGISON. TEGISON is no longer marketed in the US; for information, call Alembic Pharmaceuticals Limited at 1-866-210-9797.

Information for Pharmacists

Acitretin capsules must only be dispensed in no more than a monthly supply. An acitretin capsules Medication Guide must be given to the patient each time acitretin capsules are dispensed, as required by law.

HOW SUPPLIED

Acitretin capsules, USP are available as follows:

10 mg, opaque brown cap / opaque white body hard gelatin capsules size “4” having imprinting “A” on cap and “232” on body with black ink filled with yellow granular powder.

Bottle of 30 capsules with child resistant closure, NDC 46708-741-30

17.5 mg, opaque yellow cap / opaque yellow body hard gelatin capsules size “2” having imprinting “A” on cap and “233” on body with black ink filled with yellow granular powder.

Bottle of 30 capsules with child resistant closure, NDC 46708-742-30

25 mg, opaque brown cap / opaque yellow body hard gelatin capsules size “1” having imprinting “A” on cap and “235” on body with black ink filled with yellow granular powder.

Bottle of 30 capsules with child resistant closure, NDC 46708-743-30

Store at 25°C (77°F); excursions permitted to 15° to 30°C (59° to 86°F) [see USP Controlled Room Temperature]. Protect from light. Avoid exposure to high temperatures and humidity after the bottle is opened.

REFERENCES

1. Berbis Ph, et al.: Arch Dermatol Res (1988) 280:388-389.
2. Maier H, Honigsmann H: Concentration of etretinate in plasma and subcutaneous fat after long-term acitretin. Lancet 348:1107, 1996.
3. Geiger JM, Walker M: Is there a reproductive safety risk in male patients treated with acitretin (Neotigason/ Soriatane)? Dermatology 205:105-107, 2002.
4. Sigg C, et al.: Andrological investigations in patients treated with etretin. Dermatologica 175:48-49, 1987.
5. Parsch EM, et al.: Andrological investigation in men treated with acitretin (Ro 10-1670). Andrologia 22:479-482, 1990.
6. Kadar L, et al.: Spermatological investigations in psoriatic patients treated with acitretin. In: Pharmacology of Retinoids in the Skin; Reichert U. et al., ed, KARGER, Basel, vol. 3, pp 253-254, 1988.

The brands listed are the registered trademarks of their respective owners, and are not trademarks of Alembic Pharmaceuticals Limited.

Manufactured by:
Alembic Pharmaceuticals Limited
(Formulation Division),
Village Panelav, P. O. Tajpura, Near Baska,
Taluka-Halol, Panchmahal 389350, Gujarat, India.

Revised: 08/2024

PATIENT AGREEMENT/INFORMED CONSENT FOR FEMALE PATIENTS

To be completed by the patient* and signed by her prescriber

*Must also be initialed by the parent or guardian of a minor patient (under age 18)

Read each item below and initial in the space provided to show that you understand each item.
Do not sign this consent and do not take acitretin capsules if there is anything that you do not understand.

_______________________________________________________
(Patient’s name)

1. I understand that there is a very high risk that my unborn baby could have severe birth defects if I am pregnant or become pregnant while taking acitretin capsules in any amount even for short periods of time. Birth defects have also happened in babies of women who became pregnant after stopping treatment with acitretin capsules.

INITIAL: _____________

2. I understand that I must not become pregnant while taking acitretin capsules and for at least 3 years after the end of my treatment with acitretin capsules.

INITIAL: _____________

3. I know that I must avoid all alcohol, including drinks, food, medicines, and over-the-counter products that contain alcohol. I understand that the risk of birth defects may last longer than 3 years if I swallow any form of alcohol during therapy with acitretin capsules, and for 2 months after I stop taking acitretin capsules.

INITIAL: _____________

4. I understand that I must not have sexual intercourse, or I must use 2 separate, effective forms of birth control at the same time. The only exceptions are if I have had surgery to remove the womb (a hysterectomy) or my prescriber has told me I have gone completely through menopause.

INITIAL: ______________

5. I understand that I have to use 2 effective forms of birth control (contraception) at the same time for at least 1 month before starting acitretin capsules, for the entire time of therapy with acitretin capsules, and for at least 3 years after stopping acitretin capsules.

INITIAL: _______________

6. I understand that any form of birth control can fail. Therefore, I must use 2 different methods at the same time, every time I have sexual intercourse.

INITIAL: ________________

7. I understand that the following are considered effective forms of birth control: Primary: Tubal ligation (having my tubes tied), partner’s vasectomy, birth control pills (not progestin-only “minipills”), injectable/implantable/insertable/topical (patch) hormonal birth control products, and IUDs (intrauterine devices). Secondary: Condoms (with or without spermicide, which is a special cream or jelly that kills sperm), diaphragms and cervical caps (which must be used with a spermicide), and vaginal sponges (contains spermicide). I understand that at least 1 of my 2 methods of birth control must be a primary method.

INITIAL: ________________

8. I will talk with my prescriber about any medicines or dietary supplements I plan to take while taking acitretin capsules because certain birth control methods may not work if I am taking certain medicines or herbal products (for example, St. John’s wort).

INITIAL: _________________

9. Unless I have had a hysterectomy or my prescriber says I have gone completely through menopause, I understand that I must have 2 negative pregnancy test results before I can get a prescription to start acitretin capsules. I understand that if the second pregnancy test is negative, I must start taking my acitretin capsules within 7 days of the specimen collection. I will then have pregnancy tests on a monthly basis during therapy with acitretin capsules as instructed by my prescriber. In addition, for at least 3 years after I stop taking acitretin capsules, I will have a pregnancy test every 3 months.

INITIAL: _______________

10. I understand that I should not start taking acitretin capsules until I am sure that I am not pregnant and have negative results from 2 pregnancy tests.

INITIAL: ________________

11. I have received information on emergency contraception (birth control), including information on its availability over-the-counter.

INITIAL: _________________

12. I understand that on a monthly basis during therapy with acitretin capsules and every 3 months for at least 3 years after stopping acitretin capsules that I should receive counseling from my prescriber about contraception (birth control) and behaviors associated with an increased risk of pregnancy.

INITIAL: _________________

13. I understand that I must stop taking acitretin capsules right away and call my prescriber if I get pregnant, miss my menstrual period, stop using birth control, or have sexual intercourse without using my 2 birth control methods during and at least 3 years after stopping acitretin capsules.

INITIAL: _________________

14. If I do become pregnant while on acitretin capsules or at any time within 3 years of stopping acitretin capsules, I understand that I should report my pregnancy to Alembic Pharmaceuticals Limited at 1-800-724-4242 or to the Food and Drug Administration (FDA) MedWatch program at 1-800-fda-1088. The information I share will be kept confidential (private) unless disclosure is legally required. This will help the company and the FDA evaluate the pregnancy prevention program to prevent birth defects.

INITIAL: _________________

I have received a copy of the H.A.E.R.T. brochure. My prescriber has answered all my questions about acitretin capsules. I understand that it is my responsibility to follow my doctor’s instructions, and not to get pregnant during treatment with acitretin capsules or for at least 3 years after I stop taking acitretin capsules.

I now authorize my prescriber,______________________________________,

to begin my treatment with acitretin capsules.

Patient signature: ___________________

Date: ______________

Parent/guardian signature (if under age 18): _________________

Date: ______________________

Please print: Patient name and address:

____________________________________________

____________________________________________

Telephone:___________________________________

I have fully explained to the patient,____________________________________, the nature and purpose of the treatment described above and the risks to females of childbearing potential. I have asked the patient if she has any questions regarding her treatment with acitretin capsules and have answered those questions to the best of my ability.

Prescriber signature: _______________________________

Date: __________________________

Revised: 08/2024

MEDICATION GUIDE
Acitretin (A si TRE tin)
Capsules, USP

Read this Medication Guide carefully before you start taking acitretin capsules and read it each time you get more acitretin capsules. There may be new information.
The first information in this Medication Guide is about birth defects and how to avoid pregnancy. After this section there is important safety information about possible effects for any patient taking acitretin capsules. All patients should read this entire Medication Guide carefully. This information does not take the place of talking with your prescriber about your medical condition or treatment.

What is the most important information I should know about acitretin capsules?
Acitretin capsules can cause serious side effects, including:
• Severe birth defects. If you are a female who can get pregnant, you should use acitretin capsules only if you are not pregnant now, can avoid becoming pregnant for at least 3 years, and other medicines do not work for your severe psoriasis or you cannot use other psoriasis medicines. Information about effects on unborn babies and about how to avoid pregnancy is found in the next section: “What are the important warnings and instructions for females taking acitretin capsules?”
• Liver problems, including abnormal liver function tests and inflammation of your liver (hepatitis). Your prescriber should do blood tests to check how your liver is working before you start taking and during treatment with acitretin capsules. Stop taking acitretin capsules and call your prescriber right away if you have any of the following signs or symptoms of a serious liver problem:
o yellowing of your skin or the whites of your eyes
o nausea and vomiting
o loss of appetite
o dark urine
What are the important warnings and instructions for females taking acitretin capsules?
• Before you receive your first prescription for acitretin capsules, you should have discussed and signed a Patient Agreement/Informed Consent for Female Patients form with your prescriber. This is to help make sure you understand the risk of birth defects and how to avoid getting pregnant. If you did not talk to your prescriber about this and sign the form, contact your prescriber.
Important: If you are a female who can become pregnant:
• You must not take acitretin capsules if you are pregnant or might become pregnant during treatment or at any time for at least 3 years after you stop treatment because acitretin capsules can cause severe birth defects.
• During treatment with acitretin capsules and for 2 months after you stop treatment with acitretin capsules, you must avoid drinks, foods, and all medicines that contain alcohol. This includes over-the-counter products that contain alcohol. Avoiding alcohol is very important, because alcohol changes acitretin capsules into a drug that may take longer than 3 years to leave your body. The chance of birth defects may last longer than 3 years if you swallow any form of alcohol during treatment with acitretin capsules and for 2 months after you stop taking acitretin capsules.
• You and your prescriber must be sure you are not pregnant before you start therapy with acitretin capsules. You must have negative results from 2 pregnancy tests before you start treatment with acitretin capsules. A negative result shows you are not pregnant. Because it takes a few days after pregnancy begins for a test to show that you are pregnant, the first negative test may not ensure you are not pregnant. Do not start acitretin capsules until you have negative results from 2 pregnancy tests.
o The first pregnancy test (urine or blood) will be done at the time you and your prescriber decide if acitretin capsules might be right for you.
o The second pregnancy test will usually be done during the first 5 days of your menstrual period. You must start taking acitretin capsules within 7 days of when the urine or blood for the second pregnancy test is collected.
• After you start taking acitretin capsules, you must have a pregnancy test repeated each month that you are taking acitretin capsules. This is to be sure that you are not pregnant during treatment because acitretin capsules can cause birth defects. In addition, your prescription of acitretin capsules will be limited to a monthly supply.
• For at least 3 years after stopping treatment with acitretin capsules, you must have a pregnancy test repeated every 3 months to make sure that you are not pregnant.
• Discuss effective birth control (contraception) with your prescriber. You must use 2 effective forms of birth control (contraception) at the same time during all of the following:
o for at least 1 month before beginning treatment with acitretin capsules
o during treatment with acitretin capsules
o for at least 3 years after stopping treatment with acitretin capsules
• If you are sexually active, you must use 2 effective forms of birth control (contraception) at the same time even if you think you cannot become pregnant, unless 1 of the following is true for you:
o You had your womb (uterus) removed during an operation (a hysterectomy).
o Your prescriber said you have gone completely through menopause (the “change of life”).
The following are considered effective forms of birth control:
Primary Forms:
o having your tubes tied (tubal ligation)
o partner’s vasectomy
o IUD (Intrauterine device)
o birth control pills that contain both estrogen and progestin (combination oral contraceptives); not progestin-only “minipills”
o hormonal birth control products that are injected, implanted, or inserted in your body
o birth control patch
Secondary Forms (use with a Primary Form):
o diaphragms with spermicide
o condoms (with or without spermicide)
o cervical caps with spermicide
o vaginal sponge (contains spermicide)
At least 1 of your 2 methods of birth control must be a primary form.
• If you have sex at any time without using 2 effective forms of birth control (contraception) at the same time, or if you get pregnant or miss your period, stop using acitretin capsules and call your prescriber right away.
• Consider “Emergency Contraception” (EC) if you have sex with a male without correctly using 2 effective forms of birth control (contraception) at the same time. EC is also called “emergency birth control” which includes the “morning after” pill. Contact your prescriber as soon as possible if you have sex without using 2 effective forms of birth control (contraception) at the same time, because EC works best if it is used within 1 or 2 days after sex. EC is not a replacement for your usual 2 effective forms of birth control (contraception) because it is not as effective as regular birth control methods.
Contact your prescriber, women’s health centers, pharmacies, or hospital emergency rooms for information on how to get emergency contraception. A 24-hour, toll-free number (1-866-210-9797) is also available for patients to receive automated birth control and emergency contraception information.
• Stop taking acitretin capsules right away and contact your prescriber if you get pregnant while taking acitretin capsules or at any time for at least 3 years after treatment has stopped. You need to discuss the possible effects on the unborn baby with your prescriber.
• If you do become pregnant while taking acitretin capsules or at any time for at least 3 years after stopping acitretin capsules, you should report your pregnancy to Alembic Pharmaceuticals Limited at 1-866-210-9797 or directly to the Food and Drug Administration (FDA) MedWatch program at 1-800-FDA-1088. Your name will be kept in private (confidential). The information you share will help the FDA and the manufacturer evaluate the Pregnancy Prevention Program for acitretin capsules.
• Do not take acitretin capsules if you are breastfeeding. Acitretin can pass into your milk and may harm your baby. You will need to choose either to breast feed or take acitretin capsules, but not both.
What should males know before taking acitretin capsules?
Small amounts of acitretin are found in the semen of males taking acitretin capsules. Based upon available information, it appears that these small amounts of acitretin in semen pose little, if any, risk to an unborn child while a male patient is taking the drug or after it is discontinued. Discuss any concerns you have about this with your prescriber.
All patients should read the rest of this Medication Guide.

What are acitretin capsules?
Acitretin capsules are a medicine used to treat severe forms of psoriasis in adults. Psoriasis is a skin disease that causes cells in the outer layer of the skin to grow faster than normal and pile up on the skin’s surface. In the most common type of psoriasis, the skin becomes inflamed and produces red, thickened areas, often with silvery scales.
Because acitretin capsules can have serious side effects, you should talk with your prescriber about whether possible benefits of acitretin capsules outweigh its possible risks.
Acitretin capsules may not work right away. You may have to wait 2 to 3 months before you get the full benefit of acitretin capsules. Psoriasis gets worse for some patients when they first start treatment with acitretin capsules.
Acitretin capsules have not been studied in children.

Who should not take acitretin capsules?
• Do NOT take acitretin capsules if you can get pregnant. Do not take acitretin capsules if you are pregnant or might get pregnant during treatment with acitretin capsules or at any time for at least 3 years after you stop treatment with acitretin capsules (see “What are the important warnings and instructions for females taking acitretin capsules?”).
• Do NOT take acitretin capsules if you are breastfeeding. Acitretin can pass into your milk and may harm your baby. You will need to choose either to breast feed or take acitretin capsules, but not both.
• Do NOT take acitretin capsules if you have severe liver or kidney disease.
• Do NOT take acitretin capsules if you have repeated high blood lipids (fat in the blood).
• Do NOT take acitretin capsules if you take these medicines:
o methotrexate
o tetracyclines
The use of these medicines with acitretin capsules may cause serious side effects.
• Do NOT take acitretin capsules if you are allergic to acitretin, the active ingredient in acitretin capsules, to any of the other ingredients in acitretin capsules (see the end of this Medication Guide for a list of all the ingredients in acitretin capsules), or to any medicines that are like acitretin capsules. Ask your prescriber or pharmacist if any medicines you are allergic to are like acitretin capsules.

Before taking acitretin capsules, tell your prescriber about all your medical conditions, including if you have or have had:
• diabetes or high blood sugar
• liver problems
• kidney problems
• high cholesterol or high triglycerides (fat in the blood)
• heart disease
• depression
• alcoholism
• an allergic reaction to a medication
Your prescriber needs this information to decide if acitretin capsules are right for you and to know what dose is best for you.
Tell your prescriber about all the medicines you take, including prescription and over-the-counter medicines, vitamins, and herbal supplements.
Some medicines can cause serious side effects if taken while you also take acitretin capsules. Some medicines may affect how acitretin capsules works, or acitretin capsules may affect how other medicines work.
Be especially sure to tell your prescriber if you are taking the following medicines:
• methotrexate
• tetracyclines
• glyburide
• phenytoin
• vitamin A supplements
• progestin-only oral contraceptives (“minipills”)
• TEGISON or TIGASON (etretinate). Tell your prescriber if you have ever taken this medicine in the past.
• St. John’s wort herbal supplement
Tell your prescriber if you are getting phototherapy treatment. Your doses of phototherapy may need to be changed to prevent a burn.

How should I take acitretin capsules?
• Take acitretin capsules with food.
• Be sure to take your medicine as prescribed by your prescriber. The dose of acitretin capsules varies from patient to patient. The number of capsules you must take is chosen specially for you by your prescriber. This dose may change during treatment.
• If you miss a dose, do not double the next dose. Skip the missed dose and resume your normal schedule.
• If you take too much acitretin capsules (overdose), call your local poison control center or emergency room.
You should have blood tests for liver function, cholesterol, and triglycerides before starting treatment and during treatment to check your body’s response to acitretin capsules. Your prescriber may also do other tests.
Once you stop taking acitretin capsules, your psoriasis may return. Do not treat this new psoriasis with leftover acitretin capsules. It is important to see your prescriber again for treatment recommendations because your situation may have changed.

What should I avoid while taking acitretin capsules?
• Avoid pregnancy. See “What is the most important information I should know about acitretin capsules?”, and “What are the important warnings and instructions for females taking acitretin capsules?”
• Avoid breastfeeding. See “What are the important warnings and instructions for females taking acitretin capsules?”
• Avoid alcohol. Females who are able to become pregnant must avoid drinks, foods, medicines, and over-the-counter products that contain alcohol. The risk of birth defects may continue for longer than 3 years if you swallow any form of alcohol during treatment with acitretin capsules and for 2 months after stopping acitretin capsules (see “What are the important warnings and instructions for females taking acitretin capsules?”).
• Avoid giving blood. Do not donate blood while you are taking acitretin capsules and for at least 3 years after stopping treatment with acitretin capsules. Acitretin capsules in your blood can harm an unborn baby if your blood is given to a pregnant woman. Acitretin capsules do not affect your ability to receive a blood transfusion.
• Avoid progestin-only birth control pills (“minipills”). This type of birth control pill may not work while you take acitretin capsules. Ask your prescriber if you are not sure what type of pills you are using.
• Avoid night driving if you develop any sudden vision problems. Stop taking acitretin capsules and call your prescriber if this occurs (see “What are the possible side effects of acitretin capsules?”).
• Avoid non-medical ultraviolet (UV) light. Acitretin capsules can make your skin more sensitive to UV light. Do not use sunlamps, and avoid sunlight as much as possible. If you are taking light treatment (phototherapy), your prescriber may need to change your light dosages to avoid burns.
• Avoid dietary supplements containing vitamin A. Acitretin capsules is related to vitamin A. Therefore, do not take supplements containing vitamin A, because they may add to the unwanted effects of acitretin capsules. Check with your prescriber or pharmacist if you have any questions about vitamin supplements.
• Do not share acitretin capsules with anyone else, even if they have the same symptoms. Your medicine may harm them or their unborn child.

What are the possible side effects of acitretin capsules?
Acitretin capsules can cause serious side effects, including:
• See “What is the most important information I should know about acitretin capsules?” and “What are the important warnings and instructions for females taking acitretin capsules?”
Stop taking acitretin capsules and call your prescriber right away if you get the following signs or symptoms of possible serious side effects:
• Bad headaches, nausea, vomiting, blurred vision. These symptoms can be signs of increased brain pressure that can lead to blindness or even death.
• Vision problems. Decreased vision in the dark (night blindness). Since this can start suddenly, you should be very careful when driving at night. This problem usually goes away when treatment with acitretin capsules stops. Stop taking acitretin capsules and call your prescriber if you develop any vision problems or eye pain.
• Depression. There have been some reports of patients developing mental problems including a depressed mood, aggressive feelings, or thoughts of ending their own life (suicide). These events, including suicidal behavior, have been reported in patients taking other drugs similar to acitretin capsules as well as patients taking acitretin capsules. Since other things may have contributed to these problems, it is not known if they are related to acitretin capsules.
• Aches or pains in your bones, joints, muscles, or back, trouble moving, or loss of feeling in your hands or feet. These can be signs of abnormal changes to your bones or muscles.
• Frequent urination, great thirst or hunger. Acitretin capsules can affect blood sugar control, even if you do not already have diabetes. These are some of the signs of high blood sugar.
• Shortness of breath, dizziness, nausea, chest pain, weakness, trouble speaking, or swelling of a leg. These may be signs of a heart attack, blood clots, or stroke. Acitretin capsules can cause serious changes in blood fats (lipids). It is possible for these changes to cause blood vessel blockages that lead to heart attacks, strokes, or blood clots.
• Blood vessel problems. Acitretin capsules can cause fluid to leak out of your blood vessels into your body tissues. Call your prescriber right away if you have any of the following symptoms: sudden swelling in one part of your body or all over your body, weight gain, fever, lightheadedness or feeling faint, or muscle aches. If this happens, your prescriber will tell you to stop taking acitretin capsules.
• Serious allergic reactions. See “Who should not take acitretin capsules?” Serious allergic reactions can happen during treatment with acitretin capsules. Call your prescriber right away if you get any of the following symptoms of an allergic reaction: hives, itching, swelling of your face, mouth, or tongue, or problems breathing. If this happens, stop taking acitretin capsules and do not take it again.
• Serious skin problems. Acitretin capsules can cause skin problems that can begin in a small area and then spread over large areas of your body. Call your prescriber right away if your skin becomes red and swollen (inflamed), you have peeling of your skin, or your skin becomes itchy and painful. You should stop acitretin capsules if this happens.
Common side effects
If you develop any of these side effects or any unusual reaction, check with your prescriber to find out if you need to change the amount of acitretin capsules you take. These side effects usually get better if the dose of acitretin capsules is reduced or acitretin capsules are stopped.
• Chapped lips, peeling fingertips, palms, and soles, itching, scaly skin all over, weak nails, sticky or fragile (weak) skin, runny or dry nose, or nosebleeds. Your prescriber or pharmacist can recommend a lotion or cream to help treat drying or chapping.
• Dry mouth
• Joint pain
• Tight muscles
• Hair loss. Most patients have some hair loss, but this condition varies among patients. No one can tell if you will lose hair, how much hair you may lose or if and when it may grow back. You may also lose your eyelashes.
• Dry eyes. Acitretin capsules may dry your eyes. Wearing contact lenses may be uncomfortable during and after treatment with acitretin capsules because of the dry feeling in your eyes. If this happens, remove your contact lenses and call your prescriber. Also read the section about vision problems under “Serious side effects”.
• Rise in blood fats (lipids). Acitretin capsules can cause your blood fats (lipids) to rise. Most of the time this is not serious. But sometimes the increase can become a serious problem (see information under “Serious side effects”). You should have blood tests as directed by your prescriber.
Psoriasis gets worse for some patients when they first start treatment with acitretin capsules. Some patients have more redness or itching. If this happens, tell your prescriber. These symptoms usually get better as treatment continues, but your prescriber may need to change the amount of your medicine.
These are not all the possible side effects of acitretin capsules. For more information, ask your prescriber or pharmacist.
Call your doctor for medical advice about side effects. You may report side effects to FDA at 1-800-FDA-1088.

How should I store acitretin capsules?
• Store acitretin capsules at 25oC (77oF); excursions permitted to 15o to 30oC (59o to 86oF).
• Keepacitretin capsules away from sunlight, high temperature, and humidity.
• Acitretin capsules come in a child-resistant package.
Keep acitretin capsules and all medicines out of the reach of children.

General information about the safe and effective use of acitretin capsules
Medicines are sometimes prescribed for purposes other than those listed in a Medication Guide. Do not use acitretin capsules for a condition for which it was not prescribed. Do not give acitretin capsules to other people, even if they have the same symptoms that you have. It may harm them. You can ask your pharmacist or healthcare provider for information about acitretin capsules that is written for health professionals.

What are the ingredients in acitretin capsules?
Active ingredient: acitretin
Inactive ingredients: microcrystalline cellulose, maltodextrin, sodium ascorbate, sodium lauryl sulfate, colloidal silicon dioxide and magnesium stearate.
Gelatin capsule shells contain gelatin, iron oxide yellow, iron oxide red, titanium dioxide and sodium lauryl sulfate. Additionally, 10 mg and 25 mg gelatin capsule shells contains iron oxide black.
The gelatin capsule shells are printed with edible black ink containing shellac, iron oxide black and potassium hydroxide.
The brands listed are the registered trademarks of their respective owners, and are not trademarks of Alembic Pharmaceuticals Limited.
Manufactured by:
Alembic Pharmaceuticals Limited
(Formulation Division),
Village Panelav, P. O. Tajpura, Near Baska,
Taluka-Halol, Panchmahal 389350, Gujarat, India.

This Medication Guide has been approved by the U.S. Food and Drug Administration Revised: 08/2024

PACKAGE LABEL.PRINCIPAL DISPLAY PANEL -10 mg

NDC 46708-741-30
Acitretin
Capsules, USP
10 mg
PHARMACIST: PROVIDE A MEDICATION GUIDE WITH
EACH PRESCRIPTION. DO NOT COVER LOT AND EXPIRY.
Rx only
30 Capsules
Alembic

PACKAGE LABEL.PRINCIPAL DISPLAY PANEL - 17.5 mg

NDC 46708-742-30
Acitretin
Capsules, USP
17.5 mg
PHARMACIST: PROVIDE A MEDICATION GUIDE WITH
EACH PRESCRIPTION. DO NOT COVER LOT AND EXPIRY.
Rx only
30 Capsules
Alembic

PACKAGE LABEL.PRINCIPAL DISPLAY PANEL - 25 mg

NDC 646708-743-30
Acitretin
Capsules, USP
25 mg
PHARMACIST: PROVIDE A MEDICATION GUIDE WITH
EACH PRESCRIPTION. DO NOT COVER LOT AND EXPIRY.
Rx only
30 Capsules
Alembic